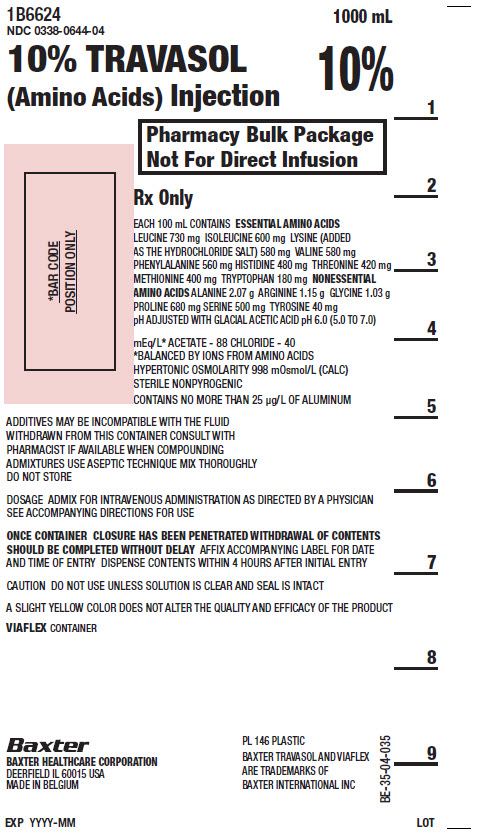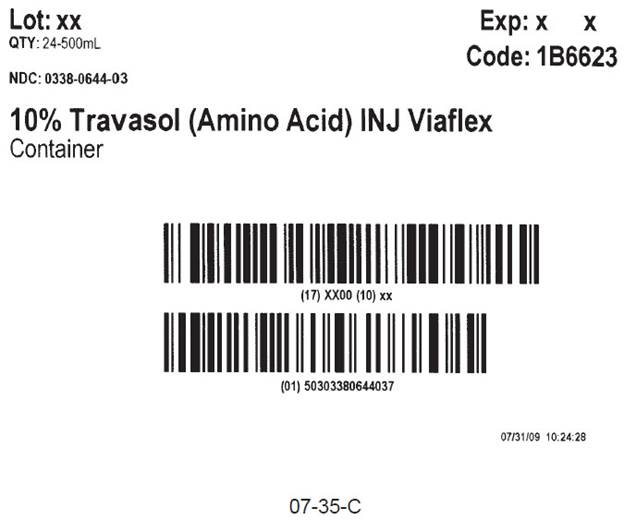 DRUG LABEL: Travasol
NDC: 0338-0644 | Form: INJECTION
Manufacturer: Baxter Healthcare Corporation
Category: prescription | Type: HUMAN PRESCRIPTION DRUG LABEL
Date: 20201007

ACTIVE INGREDIENTS: LEUCINE 730 mg/100 mL; PHENYLALANINE 560 mg/100 mL; LYSINE HYDROCHLORIDE 580 mg/100 mL; METHIONINE 400 mg/100 mL; ISOLEUCINE 600 mg/100 mL; VALINE 580 mg/100 mL; HISTIDINE 480 mg/100 mL; THREONINE 420 mg/100 mL; TRYPTOPHAN 180 mg/100 mL; ALANINE 2.07 g/100 mL; GLYCINE 1.03 g/100 mL; ARGININE 1.15 g/100 mL; PROLINE 680 mg/100 mL; TYROSINE 40 mg/100 mL; SERINE 500 mg/100 mL
INACTIVE INGREDIENTS: ACETIC ACID; WATER

HIGHLIGHTS OF PRESCRIBING INFORMATION

These highlights do not include all the information needed to use TRAVASOL safely and effectively. See full prescribing information for TRAVASOL.
TRAVASOL (amino acids) injection, for intravenous use
Initial U.S. Approval: 1984

RECENT MAJOR CHANGES

Dosage and Administration, Preparation Instructions for

Admixing Using a Parenteral Nutrition Container (2.3) 09/2020

1 INDICATIONS AND USAGE

TRAVASOL is indicated as a source of amino acids for patients requiring parenteral nutrition when oral or enteral nutrition is not possible, insufficient, or contraindicated. TRAVASOL may be used to treat negative nitrogen balance in patients. (1)

2 DOSAGE AND ADMINISTRATION

- Pharmacy Bulk Package. Not for direct intravenous infusion. (2.1)
- See full prescribing information for information on preparation, administration, instructions for use, dosing considerations, including the recommended dosage in adults and pediatrics, and dosage modifications in patients with renal impairment. (2.1, 2.2, 2.3, 2.4, 2.5, 2.6, 2.7, 2.8)
- Protect the admixed parenteral nutrition solution from light. (2.3)

3 DOSAGE FORMS AND STRENGTHS

Injection: 10% (0.1 grams/mL), 10 grams of amino acid solution per 100 mL in 500 mL, 1000 mL, and 2000 mL flexible containers. (3)

4 CONTRAINDICATIONS

- Known hypersensitivity to one or more amino acids. (4)
- Inborn errors of amino acid metabolism. (4)
  Patients with pulmonary edema or acidosis due to low cardiac output. (4)

5 WARNINGS AND PRECAUTIONS

- Pulmonary Embolism due to Pulmonary Vascular Precipitates: if signs of pulmonary distress occur, stop the infusion and initiate a medical evaluation. (5.1)
- Hypersensitivity Reactions: monitor for signs and symptoms and discontinue infusion if reactions occur. (5.2)
- Risk of Infections, Refeeding Complications, and Hyperglycemia or Hyperosmolar Hyperglycemic State: monitor for signs and symptoms; monitor laboratory parameters. (5.3, 5.4, 5.5)
- Vein Damage and Thrombosis: solutions with osmolarity of 900 mOsm/L or more must be infused through a central catheter. (2.2, 5.6)
- Hepatobiliary Disorders: monitor liver function parameters and ammonia levels. (5.7)
- Aluminum Toxicity: increased risk in patients with renal impairment, including preterm infants. (5.8, 8.4)
- Parenteral Nutrition Associated Liver Disease: increased risk in patients who receive parenteral nutrition for extended periods of time, especially preterm infants; monitor liver function tests, if abnormalities occur consider discontinuation or dosage reduction. (5.9, 8.4)
- Electrolyte Imbalance and Fluid Overload: patients with cardiac insufficiency or renal impairment may require adjustment of fluid, protein and electrolyte content. (5.10, 8.4)

6 ADVERSE REACTIONS

Adverse reactions include pulmonary vascular emboli, hypersensitivity reactions infection, refeeding syndrome, hyperglycemia and hyperosmolar hyperglycemic state, vein thrombosis, elevated liver function tests, hyperammonemia, electrolyte imbalances, and hypervolemia. (6)

To report SUSPECTED ADVERSE REACTIONS, contact Baxter Healthcare Corporation at 1-866-888-2472 or FDA at 1-800-FDA-1088 or www.fda.gov/medwatch.

8 USE IN SPECIFIC POPULATIONS

Pediatric Use: increased risk of hypoglycemia/hyperglycemia: monitor serum glucose concentrations. (8.4)

FULL PRESCRIBING INFORMATION

1 INDICATIONS AND USAGE

TRAVASOL is indicated as a source of amino acids for patients requiring parenteral nutrition when oral or enteral nutrition is not possible, insufficient, or contraindicated. TRAVASOL may be used to treat negative nitrogen balance in patients.

2 DOSAGE AND ADMINISTRATION

2.1 Important Preparation Information

TRAVASOL is supplied as a pharmacy bulk package for admixing only and is not for direct intravenous infusion. Prior to administration, TRAVASOL must be transferred to a separate parenteral nutrition container, diluted and used as an admixture with or without dextrose, electrolytes and/or lipid emulsion.

- The key factor in preparation is careful aseptic technique to avoid inadvertent touch contamination during mixing of solutions and addition of other nutrients.
- Do not remove container from overpouch until ready to use.
- Tear protective overpouch across top at slit and remove solution container. Small amounts of moisture may be found on the solution container from water permeating from inside the container. The amount of permeated water is insufficient to affect the solution significantly. If larger amounts of water are found, the container should be checked for tears or leaks.
- Inspect TRAVASOL prior to use. Some opacity of the plastic due to moisture absorption during the sterilization process may be observed. This is normal and does not affect the solution quality or safety. The opacity will diminish gradually.
Evaluate the following:
  - If the outlet port protector is damaged, detached, or not present, discard container as solution path sterility may be impaired.
  - Check to ensure the solution is clear, colorless or slightly yellow. Discard if the solution is bright yellow or yellowish brown.
  - Check for minute leaks by squeezing inner container. If leaks are found, discard container.
- TRAVASOL is intended for use in the preparation of sterile, intravenous admixtures. Because additives may be incompatible with TRAVASOL, evaluate all additions for compatibility.

2.2 Administration Instructions

TRAVASOL is for admixing use only. It is not for direct intravenous infusion. Prior to administration, TRAVASOL must be diluted with other compatible intravenous fluids or used as an admixture with or without dextrose, electrolytes and/or lipid emulsion.

- TRAVASOL is to be used only in a suitable work area such as a laminar flow hood (or an equivalent clean air compounding area). The key factor in the preparation is careful aseptic technique to avoid inadvertent touch contamination during mixing of solutions and addition of other nutrients.
- TRAVASOL is for admixing with dextrose injection and/or lipid emulsions using a parenteral nutrition container.
- When TRAVASOL is admixed with dextrose injection and/or lipid emulsion, the choice of a central or peripheral venous route should depend on the osmolarity of the final infusate. Solutions with greater than 5% dextrose or with osmolarity of 900 mOsm/L or greater must be infused through a central venous catheter [see Warnings and Precautions (5.6)].
- Use a dedicated line for parenteral nutrition solutions.
- Intravenous lipid emulsions can be infused concurrently into the same vein as TRAVASOL-dextrose solutions by a Y-connector located near the infusion site; flow rates of each solution should be controlled separately by infusion pumps.
- For administration without lipid emulsion, use a 0.22 micron in-line filter. If lipid emulsion is also administered, use a 1.2 micron in-line filter
- To prevent air embolism, use a non-vented infusion set or close the vent on a vented set, avoid multiple connections, do not connect flexible containers in series, fully evacuate residual gas in the container prior to administration, do not pressurize the flexible container to increase flow rates, and if administration is controlled by a pumping device, turn off pump before the container runs dry.
- If admixed or infused with lipid emulsion, do not use administration sets and lines that contain di-2-ethylhexyl phthalate (DEHP). Administration sets that contain polyvinyl chloride (PVC) components have DEHP as a plasticizer.
- Calcium and phosphate ratios must be considered. Excess addition of calcium and phosphate, especially in the form of mineral salts, may result in the formation of calcium phosphate precipitates [see Warnings and Precautions (5.1)].
- Prior to infusion, visually inspect the diluted parenteral nutrition solution containing TRAVASOL for particulate matter. The solution should be clear and there should be no precipitates. A slight yellow color does not alter the quality and efficacy of this product. If lipid has been added, ensure the emulsion has not separated. Separation of the emulsion can be visibly identified by a yellowish streaking or the accumulation of yellowish droplets in the mixed emulsion. Discard the admixture if any of the above are observed.

2.3 Preparation Instructions for Admixing Using a Parenteral Nutrition Container

- Open by tearing protective overwrap across top at slit and remove solution container. If overpouch has been previously opened or is damaged, discard solution.
- If the outlet port protector is damaged, detached, or not present, discard the container.
- Some opacity of the plastic due to moisture absorption during the sterilization process may be observed.
- Check for minute leaks by squeezing the inner container firmly. If leaks are found, discard solution.
- Once the protective foil overwrap has been removed, suspend container from eyelet support.
- Remove plastic protector from outlet port at bottom of container.
- Attach solution transfer set. Refer to complete directions accompanying set. Note: The closure shall be penetrated only one time with a suitable sterile transfer device or dispensing set which allows measured dispensing of the contents.
- Prepare the admixture into the parenteral nutrition container using strict aseptic techniques to avoid microbial contamination.
- Do not add the lipid emulsion to the parenteral nutrition container first; destabilization of the lipid emulsion may occur from such an admixture.
- TRAVASOL may be mixed with dextrose injection and/or lipid emulsion. The following proper mixing sequence must be followed to minimize pH related problems by ensuring that typically acidic dextrose injections are not mixed with lipid emulsions alone:
  1. Transfer dextrose injection to the parental nutrition pooling container.
  2. Transfer amino acid injection.
  3. Transfer lipid emulsion.
- Because additives may be incompatible, evaluate all additions to the parenteral nutrition container for compatibility and stability of the resulting preparation. Consult with pharmacist, if available. Questions about compatibility may be directed to Baxter. If it is deemed advisable to introduce additives to the parenteral nutrition container, use aseptic technique.
- Use gentle agitation during admixing to minimize localized concentration effects; shake containers gently after each addition.
- Alternatively, simultaneous transfer to the parenteral nutrition container of TRAVASOL, dextrose injection and lipid emulsion is also permitted.
- For admixing using an automated device, refer to Instructions for Use of the applicable device.
- The prime destabilizers of emulsions are excessive acidity (such as pH below 5) and inappropriate electrolyte content. Give careful consideration to additions of divalent cations (Ca++ and Mg++), which have been shown to cause emulsion instability. Amino acid solutions exert buffering effects that protect the emulsion.
- Inspect the final parenteral nutrition solution containing TRAVASOL to ensure that:
  - Precipitates have not formed during the mixing or addition of additives.
  - The emulsion has not separated. Separation of the emulsion can be visibly identified by a yellowish streaking or the accumulation of yellowish droplets in the admixed emulsion.
  - Discard the admixture if any of the above are observed.
- Containers should not be written on directly since ink migration has not been investigated. Affix accompanying label for date and time of entry.
  Stability and Storage
- Use for admixing should be limited to up to 4 hours at room temperature (25ºC/77ºF) after the container closure has been penetrated.
- Admixtures should be used promptly with storage under refrigeration 2° to 8°C (36° to 46°F) not to exceed 24 hours and must be completely used within 24 hours after removal from refrigeration. Any mixture remaining must be discarded.
- Protect the admixed parenteral nutrition solution from light.
- For single use only. Discard used container of TRAVASOL.

2.4 Dosing Considerations

- TRAVASOL is for admixing only. It is not for direct intravenous infusion. Prior to administration, TRAVASOL must be diluted with other compatible intravenous fluids or used as an admixture with or without dextrose, electrolytes and lipid emulsion.
- TRAVASOL is a part of the parenteral nutrition regimen which also includes dextrose, electrolytes, and lipid emulsion. Protein, caloric, fluid and electrolyte requirements all need to be taken into consideration when determining individual patient dosage needs.
- The dosage of the final parenteral nutrition solution containing TRAVASOL must be based on the concentrations of all components in the solution and the recommended nutritional requirements [see Dosage and Administration (2.5, 2.6, 2.7)]. Consult the prescribing information of all added components to determine the recommended nutritional requirements for dextrose and lipid emulsion, as applicable.
- The dosage of TRAVASOL should be individualized based on the patient’s clinical condition (ability to adequately metabolize amino acids), body weight and nutritional/fluid requirements, as well as additional energy given orally/enterally to the patient. Prior to initiating parenteral nutrition, the following patient information should be reviewed: review of all medications, gastrointestinal function and laboratory data (such as electrolytes (including magnesium, calcium, and phosphorus), glucose, urea/creatinine, liver panel, complete blood count and triglyceride level (if adding lipid emulsion)).
- Lipid emulsion administration should be considered with prolonged use (more than 5 days) of parenteral nutrition and is required in order to prevent essential fatty acid deficiency (EFAD). Serum lipids should be monitored for evidence of EFAD in patients maintained on fat-free parenteral nutrition. See complete prescribing information of lipid emulsion.
- Prior to administration of parenteral nutrition solution containing TRAVASOL, correct severe fluid, electrolyte and acid-base disorders.
- In many patients, provision of adequate calories in the form of hypertonic dextrose may require the administration of exogenous insulin to prevent hyperglycemia and glycosuria.
- Monitor levels of serum potassium during parenteral nutrition therapy. It may be necessary to add additional potassium to the parenteral nutrition admixture.

2.5 Recommended Dosage in Adults

The recommended adult daily dosage of TRAVASOL and the nutritional requirements for protein (nitrogen) are shown in Table 1.

As a component of parenteral nutrition, TRAVASOL provides 0.1 g protein/mL, which corresponds to 0.0165 g nitrogen/mL.

As indicated on an individual basis, vitamins, electrolytes, trace elements and other components (including dextrose, electrolytes and lipid emulsion) can be added to the parenteral nutrition solution to meet nutrient needs and prevent deficiencies and complications from developing.

A maximum fluid supply of 40 mL/kg/day of parenteral nutrition solution, based on protein, should not be exceeded in adult patients; this volume does not take carbohydrates or electrolytes into consideration.

The flow rate of the parenteral nutrition solution must be adjusted taking into account the dose being administered, the daily volume intake, and the duration of the infusion. The flow rate should be increased gradually and governed, especially during the first few days of therapy, by the patient’s tolerance to dextrose. Daily intake of TRAVASOL and dextrose should be increased gradually to the maximum required dose as indicated by frequent determinations of blood glucose levels.

Table 1. Recommended Daily Dosage in Adults
Adult Patient Population | Recommended Protein [Protein is provided as amino acids. When infused intravenously, amino acids are metabolized and utilized as the building blocks of protein.] Requirement (g/kg/day)1 | Corresponding Nitrogen Requirement (g/kg/day) | Recommended Daily Dosage of TRAVASOL (mL/kg/day) [A maximum fluid supply of 40 mL/kg/day of parenteral nutrition solution should not be exceeded in adult patients.]
Stable Patients | 0.8 to 1.0 | 0.13 to 0.16 | 8 to 10
Critically Ill Patients [Includes patients requiring more than 2 to 3 days in the intensive care unit with organ failure, sepsis or postoperative major surgery. Do not use in patients with conditions that are contraindicated [see Contraindications (4)].] | 1.5 to 2.0 | 0.24 to 0.32 | 15 to 20

2.6 Dosage Modifications in Patients with Renal Impairment

Prior to administration, correct severe fluid or electrolyte imbalances. Closely monitor serum electrolyte levels and adjust the volume of parenteral nutrition administered as required [see Warnings and Precautions (5.10)].

Patients with renal impairment not needing dialysis require 0.6 to 0.8 g of protein/kg/day. Serum electrolyte levels should be closely monitored. Patients on hemodialysis or continuous renal replacement therapy should receive 1.2 to 1.8 g of protein/kg/day up to a maximum of 2.5 g of protein/kg/day based on nutritional status and estimated protein losses.^2

2.7 Recommended Dosage in Pediatric Patients

The dosage and constant infusion rate of intravenous dextrose must be selected with caution in pediatric patients, particularly neonates and low weight infants, because of the increased risk of hyperglycemia/hypoglycemia [see Use in Specific Populations (8.4)]. Frequent monitoring of serum glucose concentrations is required when dextrose is prescribed to pediatric patients, particularly neonates and low birth weight infants. The infusion rate and volume should be determined by the consulting physician experienced in pediatric intravenous fluid therapy.

In pediatric patients, TRAVASOL is dosed on the basis of protein provided as amino acids. The recommended dosage, by age group is provided in Table 2.

Infusion rates are based on protein and do not take carbohydrates, fluid or electrolytes into consideration.

TRAVASOL does not contain the amino acids cysteine and taurine, considered conditionally essential for neonates and infants. If possible, these amino acids should be added to the parenteral nutrition admixture if used in this pediatric population.

Table 2. Recommended Daily Dosage in Pediatric Patients
Age | Recommended Proteina Requirement (g/kg/day)^1 | Corresponding Nitrogen Requirement (g/kg/day) | Recommended Daily Dosage of TRAVASOL (mL/kg/day)
Preterm and term infants less than 1 month of age | 3 to 4 | 0.48 to 0.64 | 30 to 40
Pediatric patients 1 month to less than 1 year of age | 2 to 3 | 0.32 to 0.48 | 20 to 30
Pediatric patients 1 to 10 years of age | 1 to 2 | 0.16 to 0.32 | 10 to 20
Pediatric patients greater than 10 to less than 17 years of age | 0.8 to 1.5 | 0.13 to 0.24 | 8 to 15
a Protein is provided as amino acids. When infused intravenously, amino acids are metabolized and utilized as the building blocks of protein.

2.8 Discontinuation of Parenteral Nutrition

To reduce the risk of hypoglycemia after discontinuation, a gradual decrease in flow rate in the last hour of infusion should be considered when administering parenteral nutrition solutions containing dextrose.

3 DOSAGE FORMS AND STRENGTHS

TRAVASOL 10% is a sterile solution of 10 grams of amino acids per 100 mL (0.1 gram/mL) available in 500 mL, 1000 mL, and 2000 mL flexible containers, which contain essential and nonessential amino acids. Table 3 describes the individual components of TRAVASOL.

Table 3. Ingredients per 100 mL of TRAVASOL
Amino Acids | 10 g
Total Nitrogen | 1.65 g
Essential Amino Acids
Leucine | 730 mg
Isoleucine | 600 mg
Lysine (added as the hydrochloride salt) | 580 mg
Valine | 580 mg
Phenylalanine | 560 mg
Histidine | 480 mg
Threonine | 420 mg
Methionine | 400 mg
Tryptophan | 180 mg
Nonessential Amino Acids
Alanine | 2.07 g
Arginine | 1.15 g
Glycine | 1.03 g
Proline | 680 mg
Serine | 500 mg
Tyrosine | 40 mg
Anion profiles per liter [Balanced by ions from amino acids.]
Acetate [Derived from pH adjustment with glacial acetic acid.] | 88 mEq
Chloride [Contributed by the Lysine Hydrochloride.] | 40 mEq
pH (Range); pH adjusted with glacial acetic acid | 6.0 (5.0 to 7.0)
Osmolarity (calc) | 998 mOsm/L

4 CONTRAINDICATIONS

The use of TRAVASOL is contraindicated in:

- Patients with known hypersensitivity to one or more amino acids [see Warnings and Precautions (5.2)].
- Patients with inborn errors of amino acid metabolism due to risk of severe metabolic or neurologic complications.
- Patients with pulmonary edema or acidosis due to low cardiac output.

5 WARNINGS AND PRECAUTIONS

5.1 Pulmonary Embolism due to Pulmonary Vascular Precipitates

Pulmonary vascular precipitates causing pulmonary vascular emboli and pulmonary distress have been reported in patients receiving parenteral nutrition, including TRAVASOL. In some cases, fatal outcomes due to pulmonary embolism have occurred. TRAVASOL contains no added phosphorus. Patients, especially those with hypophosphatemia, may require the addition of phosphate. To prevent hypocalcemia, calcium supplementation should always accompany phosphate administration. Excessive addition of calcium and phosphate increases the risk of the formation of calcium phosphate precipitates. Precipitates have been reported even in the absence of phosphate salt in the solution. Precipitation following passage through an in-line filter and suspected in vivo precipitate formation has also been reported. If signs of pulmonary distress occur, stop the infusion and initiate a medical evaluation. In addition to inspection of the solution [see Dosage and Administration (2.1, 2.2, 2.3, 2.4)], the infusion set and catheter should also periodically be checked for precipitates.

5.2 Hypersensitivity Reactions

Hypersensitivity reactions including anaphylaxis have been reported with parenteral nutrition solutions containing TRAVASOL. Stop the infusion immediately and treat patient accordingly if any signs or symptoms of a hypersensitivity reaction develop. Signs or symptoms may include: hypotension, hypertension, peripheral cyanosis, tachycardia, dyspnea, vomiting, nausea, urticaria, rash, pruritus, erythema, hyperhidrosis, pyrexia, and chills.

5.3 Risk of Infections

Patients who require parenteral nutrition are at high risk of infections because the nutritional components of these solutions can support microbial growth. Infection and sepsis may also occur as a result of the use of intravenous catheters to administer parenteral nutrition.

The risk of infection is increased in patients with malnutrition-associated immunosuppression, hyperglycemia exacerbated by dextrose infusion, long-term use and poor maintenance of intravenous catheters, or immunosuppressive effects of other concomitant conditions, drugs, or other components of the parenteral formulation (e.g., lipid emulsion).

To decrease the risk of infection, ensure aseptic technique in catheter placement and maintenance, as well as aseptic technique in the preparation and administration of the nutritional formula.

Monitor for signs and symptoms (including fever and chills) of early infections, including laboratory test results (including leukocytosis and hyperglycemia) and frequent checks of the parenteral access device and insertion site for edema, redness and discharge.

5.4 Refeeding Syndrome

Refeeding severely undernourished patients may result in refeeding syndrome, characterized by the intracellular shift of potassium, phosphorus, and magnesium as the patient becomes anabolic. Thiamine deficiency and fluid retention may also develop. To prevent these complications, monitor severely undernourished patients and slowly increase nutrient intakes.

5.5 Hyperglycemia or Hyperosmolar Hyperglycemic State

Administration of parenteral nutrition solutions containing dextrose in patients with diabetes mellitus, impaired glucose tolerance may worsen hyperglycemia. Administration of dextrose at a rate exceeding the patient’s utilization rate may lead to hyperglycemia, coma, and death. Patients with underlying confusion and renal impairment who receive dextrose infusions, may be at greater risk of developing hyperosmolar hyperglycemic state. Monitor blood glucose levels and treat hyperglycemia to maintain optimum levels while administering parenteral nutrition solutions containing dextrose. Insulin may be administered or adjusted to maintain optimal blood glucose levels during administration of parenteral nutrition solutions containing dextrose.

5.6 Vein Damage and Thrombosis

TRAVASOL must be diluted and used as an admixture with or without dextrose, electrolytes and/or lipid emulsion. It is not for direct intravenous infusion. Solutions containing more than 5% dextrose or with an osmolarity of 900 mOsm/L or greater must be infused through a central catheter [see Dosage and Administration (2.2)]. The infusion of hypertonic nutrient injections into a peripheral vein may result in vein irritation, vein damage, and/or thrombosis. The primary complication of peripheral access is venous thrombophlebitis, which manifests as pain, erythema, tenderness or a palpable cord. Remove the catheter as soon as possible, if thrombophlebitis develops.

5.7 Hepatobiliary Disorders

Hepatobiliary disorders are known to develop in some patients without preexisting liver disease who receive parenteral nutrition, including cholecystitis, cholelithiasis, cholestasis, hepatic steatosis, fibrosis and cirrhosis, possibly leading to hepatic failure. The etiology of these disorders is thought to be multifactorial and may differ between patients.

Increase in blood ammonia levels and hyperammonemia may occur in patients receiving amino acid solutions, including TRAVASOL. In some patients this may indicate hepatic insufficiency or the presence of an inborn error of amino acid metabolism [see Contraindications (4) and Use in Specific Populations (8.4)].

Monitor liver function parameters and ammonia levels. Patients developing signs of hepatobiliary disorders should be assessed early by a clinician knowledgeable in liver diseases in order to identify possible causative and contributory factors, and possible therapeutic and prophylactic interventions.

5.8 Aluminum Toxicity

TRAVASOL contains no more than 25 mcg/L of aluminum. However, with prolonged parenteral administration in patients with renal impairment, the aluminum contained in TRAVASOL may reach toxic levels. Preterm infants are at a greater risk because their kidneys are immature, and they require large amounts of calcium and phosphate solutions, which contain aluminum.

Patients with renal impairment, including preterm infants, who receive parenteral levels of aluminum at greater than 4 to 5 mcg/kg/day, accumulate aluminum at levels associated with central nervous system and bone toxicity. Tissue loading may occur at even lower rates of administration.

5.9 Risk of Parenteral Nutrition Associated Liver Disease

Parenteral Nutrition Associated Liver Disease (PNALD) has been reported in patients who receive parenteral nutrition for extended periods of time, especially preterm infants, and can present as cholestasis or steatohepatitis. The exact etiology is unknown and is likely multifactorial. If patients treated with parenteral nutrition solutions containing TRAVASOL develop liver test abnormalities, consider discontinuation or dosage reduction.

5.10 Electrolyte Imbalance and Fluid Overload

Patients with renal impairment, such as pre-renal azotemia, renal obstruction, and protein-losing nephropathy may be at increased risk of electrolyte and fluid volume imbalance. Patients with cardiac insufficiency and pulmonary congestion are susceptible to excess fluid accumulation. Use parenteral nutrition solutions containing TRAVASOL with caution in patients with cardiac insufficiency or renal impairment. The dosage of parenteral nutrition may require adjustment with specific attention to fluid, protein, and electrolyte content in these patients.

Monitor renal function parameters. Patients developing signs of renal impairment should be assessed early by a clinician knowledgeable in renal disease in order to determine the appropriate parenteral nutrition dosage and other treatment options.

5.11 Monitoring/Laboratory Tests

Monitor fluid and electrolyte status, serum osmolarity, blood glucose, liver and kidney function, blood count and coagulation parameters throughout treatment. If electrolyte levels are severely elevated, stop parenteral nutrition containing TRAVASOL until levels have been corrected.

6 ADVERSE REACTIONS

The following serious adverse reactions are discussed in greater detail in other sections of the prescribing information.

- Pulmonary embolism due to pulmonary vascular precipitates [see Warnings and Precautions (5.1)]
- Hypersensitivity reactions [see Warnings and Precautions (5.2)]
- Risk of Infections [see Warnings and Precautions (5.3)]
- Refeeding syndrome [see Warnings and Precautions (5.4)]
- Hyperglycemia or hyperosmolar hyperglycemic state [see Warnings and Precautions (5.5)]
- Vein damage and thrombosis [see Warnings and Precautions (5.6)]
- Hepatobiliary disorders [see Warnings and Precautions (5.7)]
- Aluminum toxicity [see Warnings and Precautions (5.8)]
- Parenteral Nutrition Associated Liver Disease [see Warnings and Precautions (5.9)]
- Electrolyte imbalance and fluid overload [see Warnings and Precautions (5.10)]

The following adverse reactions from voluntary reports or clinical studies have been reported with TRAVASOL. Because many of these reactions were reported voluntarily from a population of uncertain size, it is not always possible to reliably estimate their frequency or establish a causal relationship to drug exposure.

- Metabolic acidosis
- Alkalosis
- Osmotic diuresis and dehydration,
- Rebound hypoglycemia
- Hypo- and hyper-vitaminosis

8 USE IN SPECIFIC POPULATIONS

8.1 Pregnancy

Risk Summary

Limited published data with injectable amino acids solutions, including TRAVASOL in pregnant women are not sufficient to inform a drug associated risk for adverse developmental outcomes. However, malnutrition in pregnant women is associated with adverse maternal and fetal outcomes [see Clinical Considerations]. Animal reproduction studies have not been conducted with injectable amino acids solutions, including TRAVASOL.

The background risk of major birth defects and miscarriage for the indicated population is unknown. All pregnancies have a background risk of birth defect, loss, or other adverse outcomes. However, the background risk in the U.S. general population of major birth defects is 2 to 4% and of miscarriage is 15 to 20% of clinically recognized pregnancies.

Clinical Considerations

Disease-Associated Maternal and/or Embryo-Fetal Risk

Severe malnutrition in pregnant women is associated with preterm delivery, low birth weight, intrauterine growth restriction, congenital malformations and perinatal mortality. Parenteral nutrition should be considered if a pregnant woman’s nutritional requirements cannot be fulfilled by oral or enteral intake.

8.2 Lactation

Risk Summary

There are no data available to assess the presence of injectable amino acids, including TRAVASOL in human milk, the effects of TRAVASOL on the breastfed infant or the effects on milk production. The lack of clinical data during lactation precludes a clear determination of the risk of TRAVASOL to a child during lactation; therefore, the developmental and health benefits of breastfeeding should be considered along with the mother’s clinical need for TRAVASOL and any potential adverse effects on the breastfed child from TRAVASOL or from the underlying maternal condition.

8.4 Pediatric Use

Neonates, especially premature infants with low birth weight, are at increased risk of developing hypo- or hyperglycemia and therefore need close monitoring during treatment with intravenous glucose solutions to ensure adequate glycemic control in order to avoid potential long term adverse effects [see Dosage and Administration (2.7)].

Plasma electrolyte concentrations should be closely monitored in the pediatric patients who may have impaired ability to regulate fluids and electrolytes.

Hyperammonemia is of special significance in infants (birth to two years). This reaction appears to be related to a deficiency of the urea cycle amino acids of genetic or product origin. It is essential that blood ammonia be measured frequently in infants [see Warnings and Precautions (5.7)].

Because of immature renal function, preterm infants receiving prolonged parenteral nutrition treatment with TRAVASOL may be at risk of aluminum toxicity [see Warnings and Precautions (5.8)].

Patients, including pediatric patients, may be at risk for PNALD [see Warnings and Precautions (5.9)].

8.5 Geriatric Use

Clinical studies with TRAVASOL have not been performed to determine whether subjects aged 65 and over respond differently from other younger subjects. Other reported clinical experience has not identified differences in responses between the elderly and younger patients.

In general, dose selection for an elderly patient should be cautious, usually starting at the low end of the dosing range, reflecting the greater frequency of decreased hepatic, renal, or cardiac function, and of concomitant disease or drug therapy.

8.6 Renal Impairment

In patients with impaired renal function, parenteral nutrition solutions containing TRAVASOL should be administered with caution. Frequent clinical evaluation and laboratory tests to monitor renal function such as serum electrolytes (especially phosphate and potassium) and fluid balance should be conducted [see Dosage and Administration (2.6), Warnings and Precautions (5.10)].

8.7 Hepatic Impairment

In patients with impaired liver function, parenteral nutrition solutions containing TRAVASOL should be administered starting at the low end of the dosing range [see Dosage and Administration (2.5)]. Frequent clinical evaluation and laboratory tests to monitor liver function such as bilirubin and liver function parameters should be conducted [see Warnings and Precautions (5.7)].

10 OVERDOSAGE

An increased infusion rate of parenteral nutrition can cause hypervolemia, electrolyte disturbances, acidosis and/or azotemia, hyperglycemia, hyperosmolality [see Warnings and Precautions (5.5, 5.10)].

Severe hyperglycemia and severe dilutional hyponatremia, and their complications, can be fatal.

Discontinue infusion and institute appropriate corrective measures in the event of overhydration or solute overload during therapy, with particular attention to respiratory and cardiovascular systems.

For current information on the management of poisoning or overdosage, contact the National Poison Control Center at 1-800-222-1222 or www.poison.org.

11 DESCRIPTION

TRAVASOL 10% (amino acids) injection is a sterile, nonpyrogenic hypertonic solution of essential and nonessential amino acids supplied in a flexible container as a Pharmacy Bulk Package. A Pharmacy Bulk Package is a container of a sterile preparation for parenteral use that contains many single doses. The contents are intended for use in a pharmacy admixture program [see Dosage and Administration (2.1)]. TRAVASOL is not for direct intravenous infusion.

The formulas for the individual amino acids found in TRAVASOL are provided in Table 4.

Table 4. Formulas for Amino Acids
Essential Amino Acids
Leucine | (CH3)2 CHCH2CH (NH2) COOH
Isoleucine | CH3CH2CH (CH3) CH (NH2) COOH
Lysine (added as the hydrochloride salt) | H2N (CH2)4 CH (NH2) COOH
Valine | (CH3)2 CHCH (NH2) COOH
Phenylalanine | (C6H5) CH2 CH (NH2) COOH
Histidine | (C3H3N2) CH2CH (NH2) COOH
Threonine | CH3CH (OH) CH (NH2) COO
Methionine | CH3S (CH2)2 CH (NH2) COOH
Tryptophan | (C8H6N) CH2 CH (NH2) COOH
Nonessential Amino Acids
Alanine | CH3CH (NH2) COOH
Arginine | H2NC (NH) NH (CH2)3 CH (NH2) COOH
Glycine | H2NCH2COOH
Proline | [(CH2)3 NH CH] COOH
Serine | HOCH2CH (NH2) COOH
Tyrosine | [C6H4 (OH)] CH2CH (NH2) COOH

TRAVASOL contains no more than 25 mcg/L of aluminum.

12 CLINICAL PHARMACOLOGY

12.1 Mechanism of Action

TRAVASOL is used as a supplement of nutrition in patients, providing amino acids parenterally.

The amino acids provide the structural units that make up proteins and are used to synthesize proteins and other biomolecules or are oxidized to urea and carbon dioxide as a source of energy.

15 REFERENCES

1. Ayers P. et al. A.S.P.E.N. Parenteral Nutrition Handbook, 2nd ed. 2014 pg. 123
2. Mueller CM ed. The A.S.P.E.N. Nutrition Support Core Curriculum 2nd ed. 2012. Chapter 29 Wolk R, Foulks C. Renal Disease., pg. 500

16 HOW SUPPLIED/STORAGE AND HANDLING

TRAVASOL 10% (amino acids) injection is available in plastic Pharmacy Bulk Package flexible containers in the following sizes as shown in Table 5 below.

Table 5. TRAVASOL Dosage Forms
Code | Volume | NDC Number
1B6623 | 500 mL | NDC 0338-0644-03
1B6624 | 1000 mL | NDC 0338-0644-04
1B6626P | 2000 mL | NDC 0338-0644-06

Minimize exposure of TRAVASOL to heat and avoid excessive heat.

Protect from freezing.

Store TRAVASOL at room temperature (25ºC/77ºF).

Do not use if protective overpouch has been previously opened or damaged.

For storage of admixed solutions [see Dosage and Administration (2.3)].

17 PATIENT COUNSELING INFORMATION

Inform patients, caregivers, or home healthcare providers of the following risks of TRAVASOL:

- Pulmonary embolism due to pulmonary vascular precipitates [see Warnings and Precautions (5.1)]
- Hypersensitivity reactions [see Warnings and Precautions (5.2)]
- Risk of Infections [see Warnings and Precautions (5.3)]
- Refeeding syndrome [see Warnings and Precautions (5.4)]
- Hyperglycemia or hyperosmolar hyperglycemic state [see Warnings and Precautions (5.5)]
- Vein damage and thrombosis [see Warnings and Precautions (5.6)]
- Hepatobiliary disorders [see Warnings and Precautions (5.7)]
- Aluminum toxicity [see Warnings and Precautions (5.8)]
- Parenteral Nutrition Associated Liver Disease (PNALD) [see Warnings and Precautions (5.9)]
- Electrolyte imbalance and fluid overload [see Warnings and Precautions (5.10)]

Baxter Healthcare Corporation
Deerfield, IL 60015 USA

Baxter and Travasol are registered trademarks of Baxter International Inc.

PACKAGE/LABEL PRINCIPAL DISPLAY PANEL

Container Label

Container Label

1B6624 1000 mL
NDC 0338-0644-04

10% TRAVASOL
10%
(Amino Acid)
Injection

Pharmacy Bulk Package
Not For Direct Infusion

Rx Only

EACH 100mL CONTAINS ESSENTIAL AMINO ACIDS LEUCINE 730 mg
ISOLEUCINE 600 mg LYSINE(ADDED AS THE HYDROCHLORIDE SALT) 580 mg VALINE 580 mg PHENYLALANINE 560 mg HISTIDINE 480 mg
THREONINE 420 mg METHIONINE 400 mg TRYPTOPHAN 180 mg
NONESSENTIALAMINO ACIDS ALANINE 2.07 g ARGININE 1.15 g
GLYCINE 1.03 g PROLINE 680 mg SERINE 500 mg TYROSINE 40 mg
pH ADJUSTED WITH GLACIAL ACETIC ACID pH 6.0 (5.0 TO 7.0)

mEq/L* ACETATE - 88 CHLORIDE - 40
*BALANCED BY IONS FROM AMINO ACIDS
HYPERTONIC OSMOLARITY 998 mOsmo/L (CALC)
STERILE NONPYROGENIC

CONTAINS NO MORE THAN 25 µg/L OF ALUMINUM

ADDITIVES MAY BE INCOMPATIBLE WITH THE FLUID WITHDRAWN
FROM THIS CONTAINER CONSULT WITH PHARMACIST IF AVAILABLE
WHEN COMPOUNDING ADMIXTURES USE ASEPTIC TECHNIQUE
MIX THOROUGHLY DO NOT STORE

DOSAGE ADMIX FOR INTRAVENOUS ADMINISTRATION AS DIRECTED
BY A PHYSICIAN SEE ACCOMPANYING DIRECTIONS FOR USE

ONCE CONTAINER CLOSURE HAS BEEN PENETRATED
WITHDRAWAL OF CONTENTS SHOULDBE COMPLETED
WITHOUT DELAY AFFIX ACCOMPANYING LABEL FOR DATE
AND TIME OF ENTRY DISPENSE CONTENTS WITHIN 4 HOURS
AFTER INITIAL ENTRY

CAUTION DO NOT USE UNLESS SOLUTION IS CLEAR AND
SEAL IS INTACT

A SLIGHT YELLOW COLOR DOES NOT ALTER THE QUALITY AND
EFFICACY OF THE PRODUCT

VIAFLEX CONTAINER

Baxter Logo
BAXTER HEALTHCARE CORPORATION
DEERFIELD IL 60015 USA

MADE IN BELGIUM

PL 146 PLASTIC
BAXTER TRAVASOL AND VIAFLEX
ARE TRADEMARKS OF
BAXTER INTERNATIONAL INC

EXP YYYY-MM

BE-35-04-035

1 2 3 4 5 6 7 8 9

Carton Label

Carton Label

Lot: xx
Qty: 24-500mL

Exp: x x
Code: 1B6623

NDC: 0338-0644-03

10% Travasol (Amino Acid) INJ Viaflex
Container

(17) XX00 (10) xx

(01) 50303380644037

07/31/09 10:24:28

07-35-C